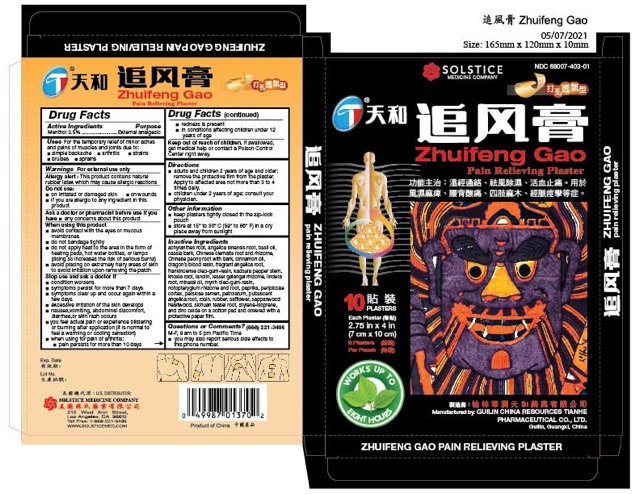 DRUG LABEL: Zhuifeng Gao Pain Relieving
NDC: 68007-403 | Form: PLASTER
Manufacturer: GUILIN CHINA RESOURCES TIANHE PHARMACEUTICAL CO LTD
Category: otc | Type: HUMAN OTC DRUG LABEL
Date: 20250926

ACTIVE INGREDIENTS: MENTHOL 35 mg/1 1
INACTIVE INGREDIENTS: ANGELICA PUBESCENS ROOT; ROSIN; NATURAL LATEX RUBBER; SAFFLOWER; BIANCAEA SAPPAN WOOD; DIPSACUS ASPER ROOT; STYRENE; ISOPRENE; ZINC OXIDE; ACHYRANTHES BIDENTATA ROOT; ANGELICA SINENSIS ROOT; OCIMUM GRATISSIMUM WHOLE; CHINESE CINNAMON; CLEMATIS CHINENSIS ROOT; PAEONIA VEITCHII ROOT; CINNAMON OIL; DRAGON'S BLOOD; ANGELICA DAHURICA ROOT; FRANKINCENSE; PIPER KADSURA STEM; KNOXIA ROXBURGHII SUBSP. BRUNONIS ROOT; LANOLIN; LESSER GALANGAL ROOT; LINDERA AGGREGATA ROOT; MINERAL OIL; MYRRH; NOTOPTERYGIUM INCISUM ROOT; PAPRIKA; PERIPLOCA SEPIUM ROOT BARK; PRUNUS PERSICA SEED; PETROLATUM

Drug Facts

Active Ingredients
Menthol 3.5%

Purpose
External Analgesic

Uses
For the temporary relief of minor aches and pains of muscles and joints due to:
■ simple backache ■ arthritis ■ strains ■ bruises ■ sprains

Warnings
For external use only

Allergy alert:This product contains natural rubber latex which may cause allergic reactions.

Do not use
■ on irritated or damaged skin
■ on wounds
■ if you are allergic to any ingredient in this product

Ask a doctor or pharmacist before use if you have
■ any concerns about using this product

When using this product
■ avoid contact with the eyes or mucous membranes
■ do not bandage tightly
■ do not apply heat to the area in form of heating pads, hot water bottles, or lamps (doing so increases the risk of serious burns)
■ avoid placing on extremely hairy areas of skin to avoid irritation upon removing the patch

Stop use and ask a doctor if
■ condition worsens
■ symptoms persist for more than 7 days
■ symptoms clear up and occur again within a few days
■ excessive irritation of the skin develops
■ nausea, vomiting, abdominal discomfort, diarrhea, or skin rash occurs
■ you feel actual pain or experience blistering or burning after application (it is normal to feel a warming or cooling sensation)
■ when using for pain of arthritis:
■ pain persists for more than 10 days
■ redness is present
■ in conditions affecting children under 12 years of age

KEEP OUT OF REACH OF CHILDREN

Keep out of reach of childrento avoid accidental poisoning. If swallowed, get medical help or contact a Poison Control Center right away.

Directions
■ adults and children 2 years of age and older: remove the protective film from the plaster. Apply to affected area not more than 3 to 4 times daily.
■ children under 2 years of age: consult your physician.

Other information
■ keep plasters tightly closed in the zip-lock pouch
■ store at 15 to 30 C (59 to 86 F) in a dry place away from sunlight

INACTIVE INGREDIENT

Inactive ingredientsachyranthes root, angelica sinensis root, basil oil, cassia bark, Chinese clematis root and rhizome, Chinese peony root with bark, cinnamon oil, dragon’s blood resin, fragrant angelica root, frankincense oleo-gum-resin, kadsura pepper stem, knoxia root, lanolin, lesser galangal rhizome, lindera root, mineral oil, myrrh oleo-gum-resin, notopterygium rhizome and root, paprika, periplocae cortex, persicae semen, petrolatum, pubescent angelica root, rosin, rubber, safflower, sappanwood heartwood, sichuan teasel root, styrene-isoprene, and zinc oxide on a cotton pad and covered with a protective paper film.

Questions or comments?
(888) 221-3496M-F 9 am to 5 pm
■ you may also report serious side effects to this phone number

PACKAGE LABEL

Zhuifeng Gao Pain Relieving Plaster
NDC 68007-403-01

10 Patches
Each Patch 2.75 in x 4 in (7 cm x 10 cm)
5 Patches per Pouch